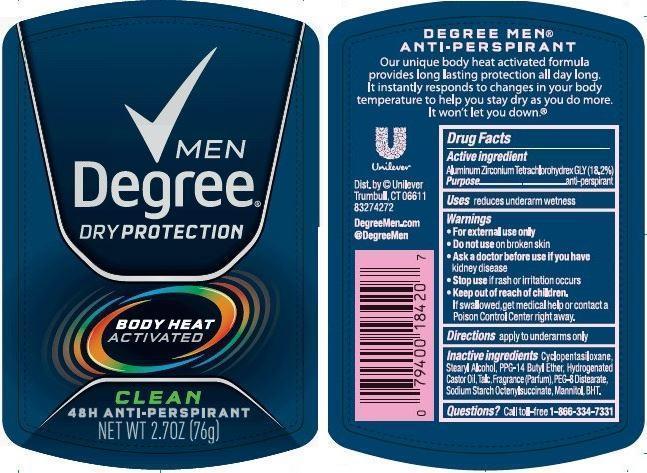 DRUG LABEL: Degree
NDC: 64942-1184 | Form: STICK
Manufacturer: Conopco Inc. d/b/a Unilever
Category: otc | Type: HUMAN OTC DRUG LABEL
Date: 20141015

ACTIVE INGREDIENTS: Aluminum Zirconium Tetrachlorohydrex GLY 18.2 g/100 g
INACTIVE INGREDIENTS: CYCLOMETHICONE 5; STEARYL ALCOHOL; PPG-14 BUTYL ETHER; HYDROGENATED CASTOR OIL; TALC; PEG-8 DISTEARATE; MANNITOL; BUTYLATED HYDROXYTOLUENE

Degree Clean antiperspirant deodorant

Active Ingredient

Aluminum Zirconium Tetrachlorohydrex GLY (18.2%)

Purpose
anti-perspirant

Warnings
• For external use only

• Do not use on broken skin

• Ask a doctor before use if you have kidney disease

• Stop use if rash or irritation occurs

• Keep out of reach of children. If swallowed, get medical help or contact a Poison Control Center right away.

INDICATIONS AND USAGE

Uses reduces underarm wetness

DOSAGE AND ADMINISTRATION

Directions apply to underarms only

INACTIVE INGREDIENT

Inactive ingredients Cyclopentasiloxane, Stearyl Alcohol, PPG-14 Butyl Ether, Hydrogenated Castor Oil, Talc, PEG-8 distearate, Fragrance (Parfum), Sodium Starch Octenylsuccinate, Mannitol, BHT.

Questions? Call toll-free 1-866-334-7331